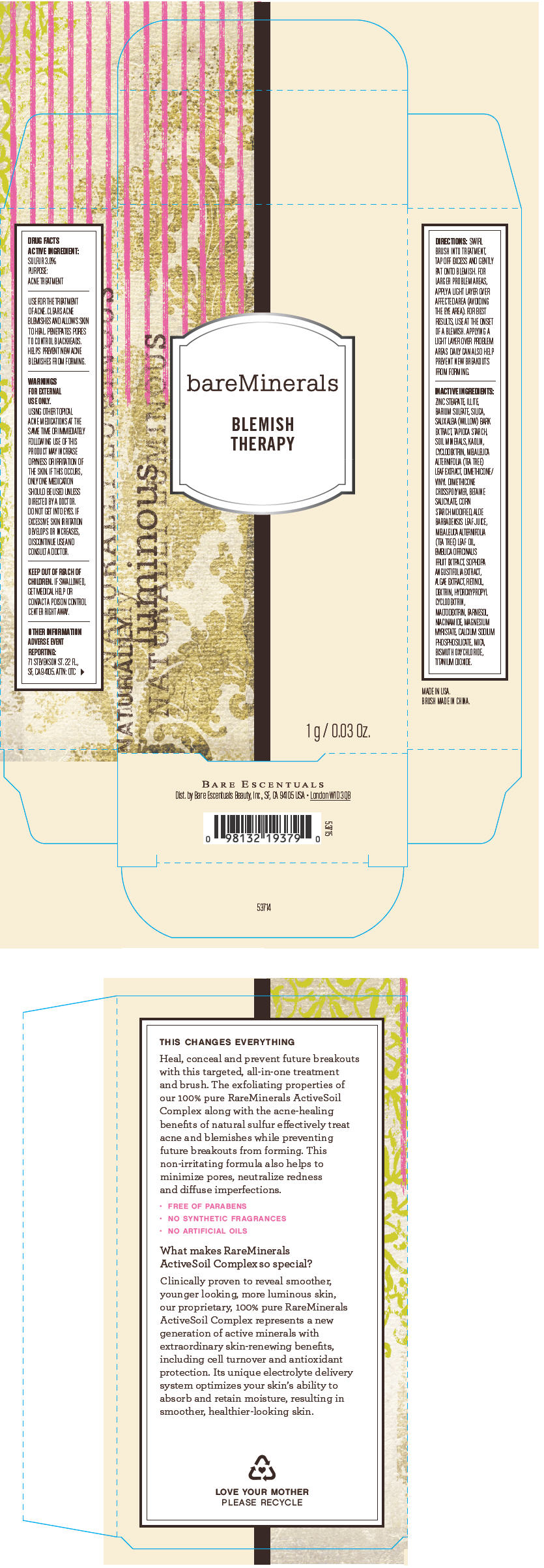 DRUG LABEL: bareMinerals Blemish Therapy
NDC: 98132-725 | Form: POWDER
Manufacturer: Bare Escentuals Beauty, Inc.
Category: otc | Type: HUMAN OTC DRUG LABEL
Date: 20140212

ACTIVE INGREDIENTS: Sulfur 30 mg/1 g
INACTIVE INGREDIENTS: ZINC STEARATE; BARIUM SULFATE; SILICON DIOXIDE; SALIX ALBA BARK; STARCH, TAPIOCA; KAOLIN; MELALEUCA ALTERNIFOLIA LEAF; BETAINE SALICYLATE; ALOE VERA LEAF; TEA TREE OIL; PHYLLANTHUS EMBLICA FRUIT; SOPHORA FLAVESCENS ROOT; RETINOL; ICODEXTRIN; MALTODEXTRIN; FARNESOL; NIACINAMIDE; MAGNESIUM MYRISTATE; MICA; BISMUTH OXYCHLORIDE; TITANIUM DIOXIDE

bareMinerals Blemish Therapy

Drug Facts

ACTIVE INGREDIENT

SULFUR 3.0%

PURPOSE

ACNE TREATMENT

INDICATIONS AND USAGE

USE FOR THE TREATMENT OF ACNE. CLEARS ACNE BLEMISHES AND ALLOWS SKIN TO HEAL. PENETRATES PORES TO CONTROL BLACKHEADS. HELPS PREVENT NEW ACNE BLEMISHES FROM FORMING.

WARNINGS

FOR EXTERNAL USE ONLY.

USING OTHER TOPICAL ACNE MEDICATIONS AT THE SAME TIME OR IMMEDIATELY FOLLOWING USE OF THIS PRODUCT MAY INCREASE DRYNESS OR IRRITATION OF THE SKIN. IF THIS OCCURS, ONLY ONE MEDICATION SHOULD BE USED UNLESS DIRECTED BY A DOCTOR.

DO NOT GET INTO EYES.

STOP USE

IF EXCESSIVE SKIN IRRITATION DEVELOPS OR INCREASES, DISCONTINUE USE AND CONSULT A DOCTOR.

KEEP OUT OF REACH OF CHILDREN. IF SWALLOWED, GET MEDICAL HELP OR CONTACT A POISON CONTROL CENTER RIGHT AWAY.

OTHER INFORMATION

ADVERSE EVENT REPORTING

71 STEVENSON ST. 22 FL., SF, CA 94105. ATTN: OTC

DIRECTIONS

SWIRL BRUSH INTO TREATMENT, TAP OFF EXCESS AND GENTLY PAT ONTO BLEMISH. FOR LARGER PROBLEM AREAS, APPLY A LIGHT LAYER OVER AFFECTED AREA (AVOIDING THE EYE AREA). FOR BEST RESULTS, USE AT THE ONSET OF A BLEMISH. APPLYING A LIGHT LAYER OVER PROBLEM AREAS DAILY CAN ALSO HELP PREVENT NEW BREAKOUTS FROM FORMING.

INACTIVE INGREDIENTS

ZINC STEARATE, ILITE, BARIUM SULFATE, SILICA, SALIX ALBA (WILOW) BARK EXTRACT, TAPI OCA STARCH, SOIL MINERALS, KA OLIN, CYCL ODEXTRIN, MELALEUCA ALTERNIF OLIA (TEA TRE) LEAF EXTRACT, DIMETHICONE/ VINYL DIMETHICONE CROSSPOLYMER, BETAINE SALICYLATE, CORN STARCH MODIFIED, ALOE BARBADENSIS LEAF JUICE, MELALEUCA ALTERNIF OLIA (TEA TRE) LEAF OIL, EMBLICA OFFICINALIS FRUIT EXTRACT, SOPHORA ANGUSTIFOLIA EXTRACT, ALGAE EXTRACT, RETINOL, DEXTRIN, HYDROXYPR OPYL CYCL ODEXTRIN, MALT ODEXTRIN, FARNE SOL, NIACINAMIDE, MAGNESIUM MYRISTATE, CALCIUM SODIUM PHOSPHOSILICATE, MICA, BISMUTH OXYCHL ORIDE, TITANIUM DIOXIDE.

Dist. by Bare Escentuals Beauty, Inc., SF, CA 94105 USA

PRINCIPAL DISPLAY PANEL - 1 g Jar Carton

bareMinerals

BLEMISH
THERAPY

1 g / 0.03 Oz.